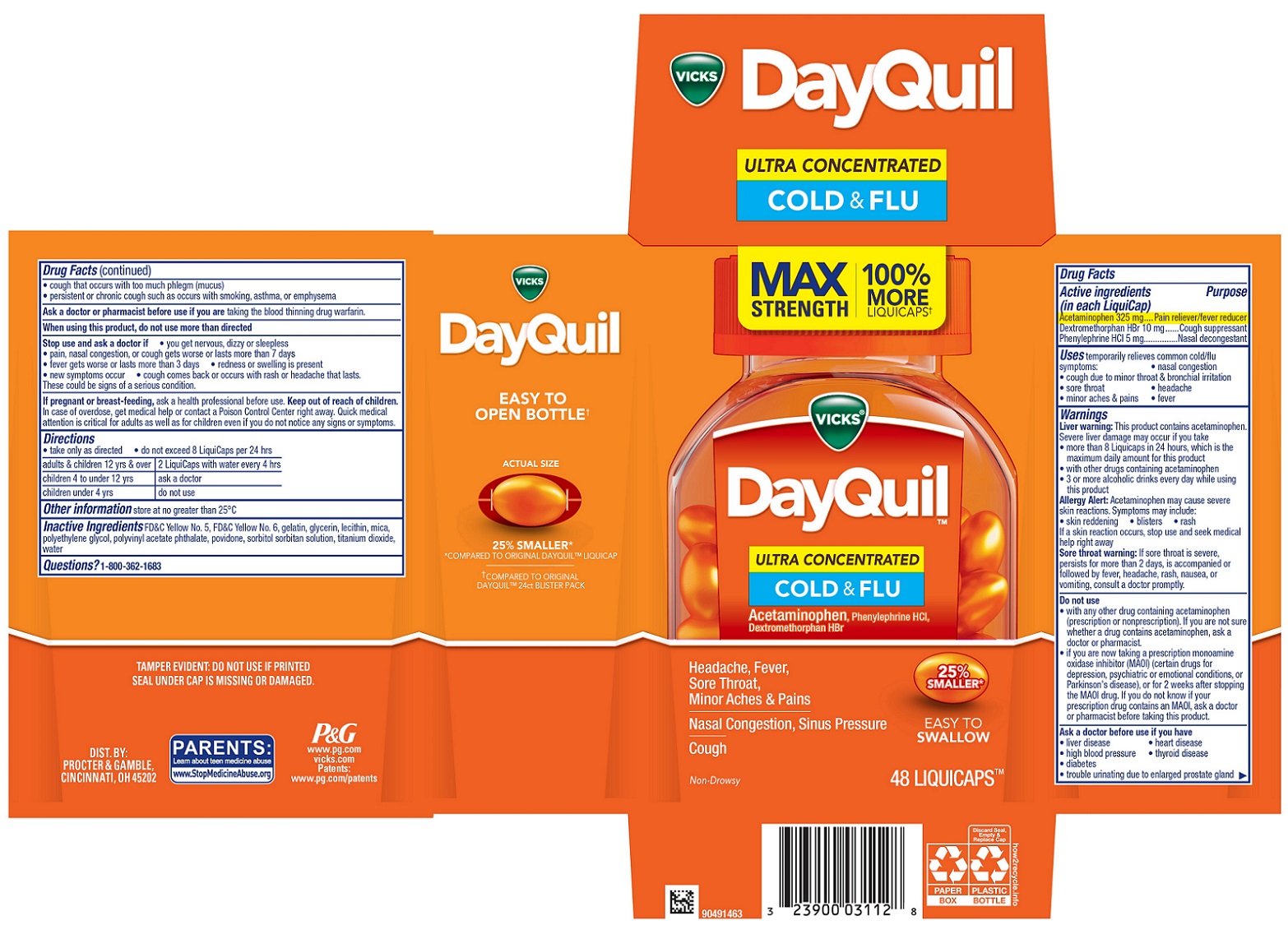 DRUG LABEL: Vicks DayQuil
NDC: 69423-800 | Form: CAPSULE, LIQUID FILLED
Manufacturer: The Procter & Gamble Manufacturing Company
Category: otc | Type: HUMAN OTC DRUG LABEL
Date: 20251106

ACTIVE INGREDIENTS: PHENYLEPHRINE HYDROCHLORIDE 5 mg/1 1; ACETAMINOPHEN 325 mg/1 1; DEXTROMETHORPHAN HYDROBROMIDE 10 mg/1 1
INACTIVE INGREDIENTS: POLYETHYLENE GLYCOL, UNSPECIFIED; POLYVINYL ACETATE PHTHALATE; WATER; SORBITOL; GLYCERIN; POVIDONE; TITANIUM DIOXIDE; MICA; FD&C YELLOW NO. 5; GELATIN; FD&C YELLOW NO. 6; LECITHIN, SOYBEAN

VICKS® DayQuil™ ULTRA CONCENTRATED COLD & FLU, LiquiCaps™

Active ingredients (in each LiquiCap)

Acetaminophen 325 mg
Dextromethorphan HBr 10 mg
Phenylephrine HCl 5 mg

Active ingredients (in each LiquiCap) Purpose

Pain reliever/fever reducer
Cough suppressant
Nasal decongestant

Uses

temporarily relieves common cold/flu symptoms:

• nasal congestion

• cough due to minor throat & bronchial irritation

• sore throat

• headache

• minor aches & pains • fever

Warnings

Liver warning:This product contains acetaminophen.
Severe liver damage may occur if you take
• more than 8 Liquicaps in 24 hours, which is the maximum daily amount for this product
• with other drugs containing acetaminophen
• 3 or more alcoholic drinks every day while using this product

Allergy Alert:Acetaminophen may cause severe skin reactions.

Symptoms may include:

• skin reddening

• blisters

• rash

If a skin reaction occurs, stop use and seek medical help right away

Sore throat warning: If sore throat is severe, persists for more than 2 days, is accompanied or followed by fever, headache, rash, nausea, or vomiting, consult a doctor promptly.

Do not use

• with any other drug containing acetaminophen (prescription or nonprescription). If you are not sure whether a drug contains acetaminophen, ask a doctor or pharmacist.
• if you are now taking a prescription monoamine oxidase inhibitor (MAOI) (certain drugs for depression, psychiatric or emotional conditions, or Parkinson's disease), or for 2 weeks after stopping the MAOI drug. If you do not know if your prescription drug contains an MAOI, ask a doctor or pharmacist before taking this product.

Ask a doctor before use if you have

• liver disease

• heart disease

• high blood pressure

• thyroid disease

• diabetes

• trouble urinating due to enlarged prostate gland

• cough that occurs with too much phlegm (mucus)

• persistent or chronic cough such as occurs with smoking, asthma, or emphysema

Ask a doctor or pharmacist before use if you are

taking the blood thinning drug warfarin.

When using this product,

do not use more than directed

Stop use and ask a doctor if

• you get nervous, dizzy or sleepless

• pain, nasal congestion, or cough gets worse or lasts more than 7 days

• fever gets worse or lasts more than 3 days

• redness or swelling is present

• new symptoms occur

• cough comes back or occurs with rash or headache that lasts.

These could be signs of a serious condition.

If pregnant or breast-feeding,

ask a health professional before use.

OVERDOSAGE

In case of overdose, get medical help or contact a Poison Control Center right away.

Quick medical attention is critical for adults as well as for children even if you do not notice any signs or symptoms.

Directions

- take only as directed
- do not exceed 8 LiquiCaps per 24 hrs

adults & children 12 yrs & over | 2 LiquiCaps with water every 4 hrs
children 4 to under 12 yrs | ask a doctor
children under 4 yrs | do not use

Other information

store at no greater than 25°C

Inactive Ingredients

FD&C Yellow No. 5, FD&C Yellow No. 6, gelatin, glycerin, lecithin, mica, polyethylene glycol, polyvinyl acetate phthalate, povidone, sorbitol sorbitan solution, titanium dioxide, water

Questions?

1-800-362-1683

TAMPER EVIDENT: DO NOT USE IF PRINTED SEAL UNDER CAP IS MISSING OR DAMAGED.

DIST. BY PROCTER & GAMBLE, CINCINNATI, OH 45202

PRINCIPAL DISPLAY PANEL - 48 LiquiCaps™

MAX STRENGTH

100% MORE LIQUICAPS†

VICKS®

DayQuil™

ULTRA CONCENTRATED

COLD & FLU

Acetaminophen, Phenylephrine HCl, Dextromethorphan HBr

Headache, Fever, Sore Throat, Minor Aches & Pains

Nasal Congestion, Sinus Pressure

Cough

Non-Drowsy

25% SMALLER*

EASY TO SWALLOW

48 LIQUICAPS™